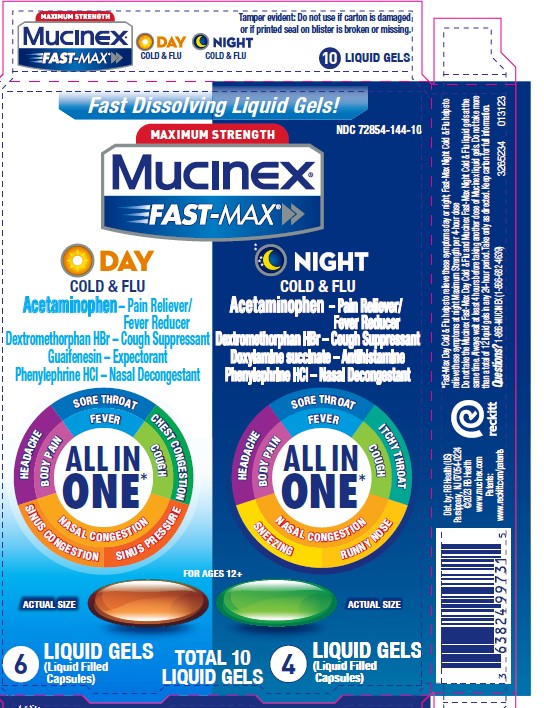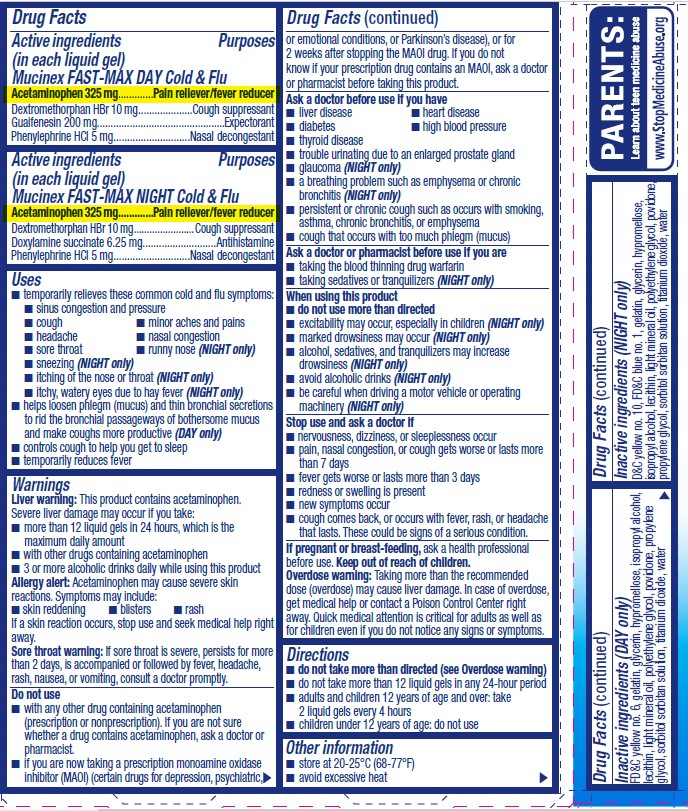 DRUG LABEL: Mucinex Fast-Max Day Cold and Flu and Night Cold and Flu
NDC: 72854-144 | Form: KIT | Route: ORAL
Manufacturer: RB Health (US) LLC
Category: otc | Type: HUMAN OTC DRUG LABEL
Date: 20241223

ACTIVE INGREDIENTS: ACETAMINOPHEN 325 mg/1 1; DEXTROMETHORPHAN HYDROBROMIDE 10 mg/1 1; GUAIFENESIN 200 mg/1 1; PHENYLEPHRINE HYDROCHLORIDE 5 mg/1 1; ACETAMINOPHEN 325 mg/1 1; DEXTROMETHORPHAN HYDROBROMIDE 10 mg/1 1; DOXYLAMINE SUCCINATE 6.25 mg/1 1; PHENYLEPHRINE HYDROCHLORIDE 5 mg/1 1
INACTIVE INGREDIENTS: FD&C YELLOW NO. 6; GELATIN, UNSPECIFIED; GLYCERIN; HYPROMELLOSE, UNSPECIFIED; ISOPROPYL ALCOHOL; LIGHT MINERAL OIL; POLYETHYLENE GLYCOL, UNSPECIFIED; POVIDONE, UNSPECIFIED; PROPYLENE GLYCOL; TITANIUM DIOXIDE; WATER; D&C YELLOW NO. 10; FD&C BLUE NO. 1; GELATIN, UNSPECIFIED; GLYCERIN; HYPROMELLOSE, UNSPECIFIED; ISOPROPYL ALCOHOL; LIGHT MINERAL OIL; POLYETHYLENE GLYCOL, UNSPECIFIED; POVIDONE, UNSPECIFIED; PROPYLENE GLYCOL; TITANIUM DIOXIDE; WATER

Mucinex® Fast-Max®Day Cold & Flu and Night Cold & Flu
Maximum Strength

Drug Facts

ACTIVE INGREDIENT

PURPOSE

Active ingredients (in each liquid gel) Mucinex FAST-MAX DAY Cold & Flu | Purposes
Acetaminophen 325 mg | Pain reliever/fever reducer
Dextromethorphan HBr 10 mg | Cough suppressant
Guaifenesin 200 mg | Expectorant
Phenylephrine HCl 5 mg | Nasal decongestant

Active ingredients (in each liquid gel) Mucinex FAST-MAX NIGHT Cold & Flu | Purposes
Acetaminophen 325 mg | Pain reliever/fever reducer
Dextromethorphan HBr 10 mg | Cough suppressant
Doxylamine succinate 6.25 mg | Antihistamine
Phenylephrine HCl 5 mg | Nasal decongestant

Uses

- temporarily relieves these common cold and flu symptoms:
  - sinus congestion and pressure
  - cough
  - minor aches and pains
  - headache
  - nasal congestion
  - sore throat
  - runny nose (NIGHT only)
  - sneezing (NIGHT only)
  - itching of the nose or throat (NIGHT only)
  - itchy, watery eyes due to hay fever (NIGHT only)
- helps loosen phlegm (mucus) and thin bronchial secretions to rid the bronchial passageways of bothersome mucus and make coughs more productive (DAY only)
- controls cough to help you get to sleep
- temporarily reduces fever

Warnings

Liver warning

This product contains acetaminophen. Severe liver damage may occur if you take:

- more than 12 liquid gels in 24 hours, which is the maximum daily amount
- with other drugs containing acetaminophen
- 3 or more alcoholic drinks daily while using this product

Allergy alert

Acetaminophen may cause severe skin reactions. Symptoms may include:

- skin reddening
- blisters
- rash

If a skin reaction occurs, stop use and seek medical help right away.

Sore throat warning

If sore throat is severe, persists for more than 2 days, is accompanied or followed by fever, headache, rash, nausea, or vomiting, consult a doctor promptly.

Do not use

- with any other drug containing acetaminophen (prescription or nonprescription). If you are not sure whether a drug contains acetaminophen, ask a doctor or pharmacist.
- if you are now taking a prescription monoamine oxidase inhibitor (MAOI) (certain drugs for depression, psychiatric, or emotional conditions, or Parkinson's disease), or for 2 weeks after stopping the MAOI drug. If you do not know if your prescription drug contains an MAOI, ask a doctor or pharmacist before taking this product.

Ask a doctor before use if you have

- liver disease
- heart disease
- diabetes
- high blood pressure
- thyroid disease
- trouble urinating due to an enlarged prostate gland
- glaucoma (NIGHT only)
- a breathing problem such as emphysema or chronic bronchitis (NIGHT only)
- persistent or chronic cough such as occurs with smoking, asthma, chronic bronchitis, or emphysema
- cough that occurs with too much phlegm (mucus)

Ask a doctor or pharmacist before use if you are

- taking the blood thinning drug warfarin
- taking sedatives or tranquilizers (NIGHT only)

When using this product

- do not use more than directed
- excitability may occur, especially in children (NIGHT only)
- marked drowsiness may occur (NIGHT only)
- alcohol, sedatives, and tranquilizers may increase drowsiness (NIGHT only)
- avoid alcoholic drinks (NIGHT only)
- be careful when driving a motor vehicle or operating machinery (NIGHT only)

Stop use and ask a doctor if

- nervousness, dizziness, or sleeplessness occur
- pain, nasal congestion, or cough gets worse or lasts more than 7 days
- fever gets worse or lasts more than 3 days
- redness or swelling is present
- new symptoms occur
- cough comes back, or occurs with fever, rash, or headache that lasts. These could be signs of a serious condition.

PREGNANCY OR BREAST FEEDING

If pregnant or breast-feeding,ask a health professional before use.

Keep out of reach of children.

Overdose warning

Taking more than the recommended dose (overdose) may cause liver damage. In case of overdose, get medical help or contact a Poison Control Center right away. Quick medical attention is critical for adults as well as for children even if you do not notice any signs or symptoms.

Directions

- do not take more than directed (see Overdose warning)
- do not take more than 12 liquid gels in any 24-hour period
- adults and children 12 years of age and over: take 2 liquid gels every 4 hours
- children under 12 years of age: do not use

Other information

- store at 20-25°C (68-77°F)
- avoid excessive heat

Inactive ingredients (DAY only)

FD&C yellow no. 6, gelatin, glycerin, hypromellose, isopropyl alcohol, lecithin, light mineral oil, polyethylene glycol, povidone, propylene glycol, sorbitol sorbitan solution, titanium dioxide, water

Inactive ingredients (NIGHT only)

D&C yellow no. 10, FD&C blue no. 1, gelatin, glycerin, hypromellose, isopropyl alcohol, lecithin, light mineral oil, polyethylene glycol, povidone, propylene glycol, sorbitol sorbitan solution, titanium dioxide, water

Questions?

1-866-MUCINEX (1-866-682-4639)

You may also report side effects to this phone number.

Dist. by: RB Health (US)
Parsippany, NJ 07054-0224

PRINCIPAL DISPLAY PANEL - Kit Carton

Fast Dissolving Liquid Gels!

NDC 72854-144-10

MAXIMUM STRENGTH
Mucinex®
FAST-MAX®

DAY
COLD & FLU

Acetaminophen– Pain Reliever/
Fever Reducer
Dextromethorphan HBr – Cough Suppressant
Guaifenesin – Expectorant
Phenylephrine HCl – Nasal Decongestant

HEADACHE
SORE THROAT
CHEST CONGESTION
BODY PAIN
FEVER
COUGH

ALL IN
ONE*

NASAL CONGESTION
SINUS CONGESTION
SINUS PRESSURE

ACTUAL SIZE

FOR AGES 12+

LIQUID GELS
(Liquid Filled
Capsules)

NIGHT
COLD & FLU

Acetaminophen – Pain Reliever/
Fever Reducer
Dextromethorphan HBr – Cough Suppressant
Doxylamine succinate – Antihistamine
Phenylephrine HCl – Nasal Decongestant

HEADACHE
SORE THROAT
ITCHY THROAT
BODY PAIN
FEVER
COUGH

ALL IN
ONE*

NASAL CONGESTION
SNEEZING
RUNNY NOSE

ACTUAL SIZE

LIQUID GELS
(Liquid Filled
Capsules)

TOTAL 10
LIQUID GELS